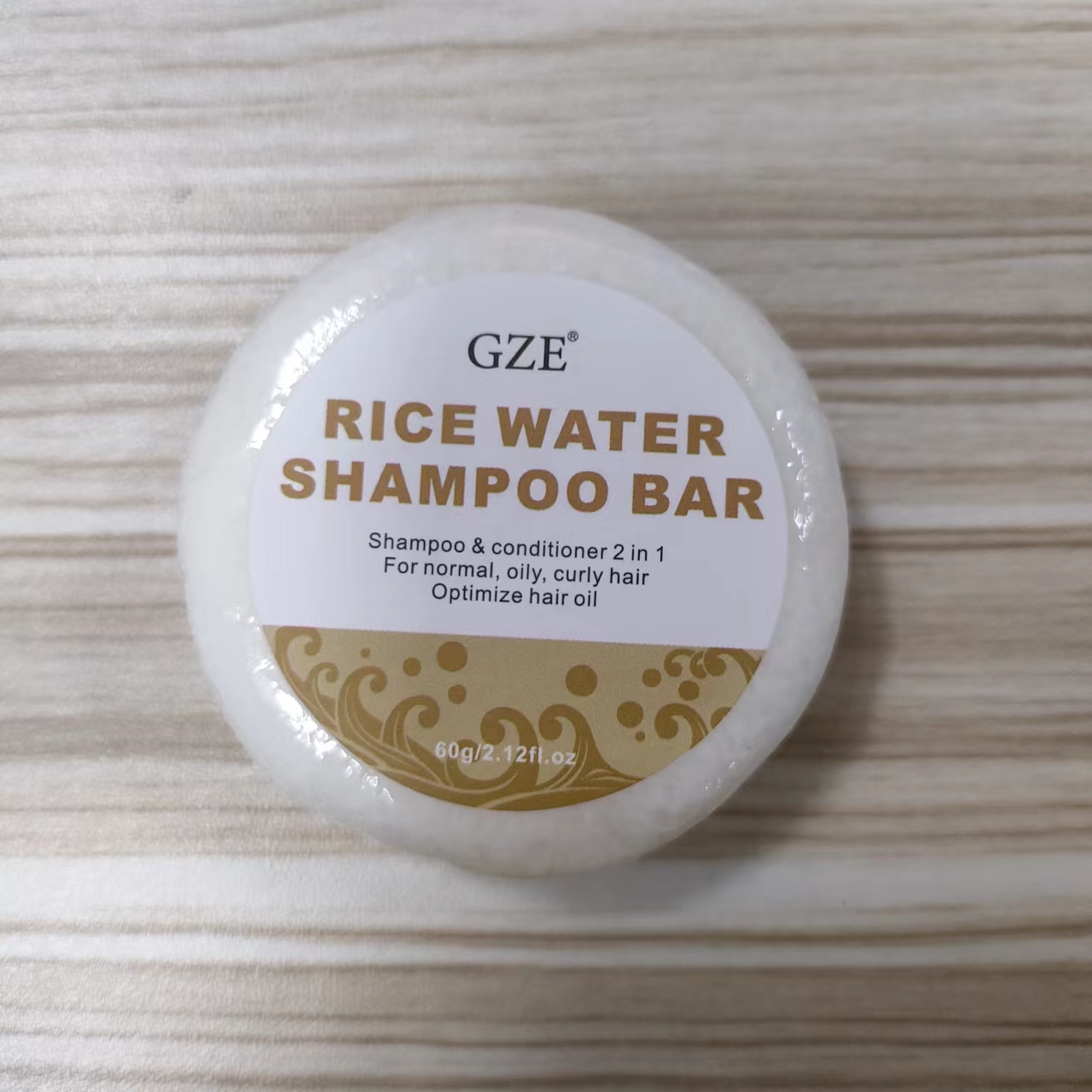 DRUG LABEL: GZE Rice Water ShampooBar
NDC: 74458-052 | Form: SOAP
Manufacturer: Guangzhou Yilong Cosmetics Co., Ltd
Category: otc | Type: HUMAN OTC DRUG LABEL
Date: 20241026

ACTIVE INGREDIENTS: LIMOSILACTOBACILLUS FERMENTUM 5 g/100 g; RICE BRAN OIL 12.5 g/100 g
INACTIVE INGREDIENTS: SODIUM COCOYL ISETHIONATE; TOCOPHEROL; ORYZA SATIVA WHOLE; OLEA EUROPAEA (OLIVE) FRUIT OIL; COCOS NUCIFERA (COCONUT) OIL; ARGANIA SPINOSA KERNEL OIL

GZE RICE WATER SHAMPOO BAR

ACTIVE INGREDIENT

Oryza Sativa (Rice) Bran Oil 12.5%

Lactobacillus Ferment 5%

INACTIVE INGREDIENT

Sodium Cocoyl Isethionate

Olea Europaea (Olive) Fruit Oil

Cocos Nucifera (Coconut) Oil

Argania Spinosa Kernel Oil

Tocopherol/Wheat Polypeptides

Oryza Sativa (Rice) Powder

PURPOSE

Clean the scalp.

INDICATIONS AND USAGE

Wet hair, dip some water on the soap, rub soap with your hands or foaming net to make a dense foam.Apply the foam on hair, gently massage scalp for 3-5minutes, rinse with water.

WARNINGS

For external use only.

Stop use and ask a doctor if rash occurs.

Do not use on damaged or broken skin.

When using this product keep out of eyes. Rinse with water to remove.

Keep out of reach of children. If swallowed, get medical help or contact a Poison Control Center right away.

DOSAGE AND ADMINISTRATION

Wet hair, dip some water on the soap, rub soap with your hands or foaming net to make a dense foam.Apply the foam on hair, gently massage scalp for 3-5minutes, rinse with water.